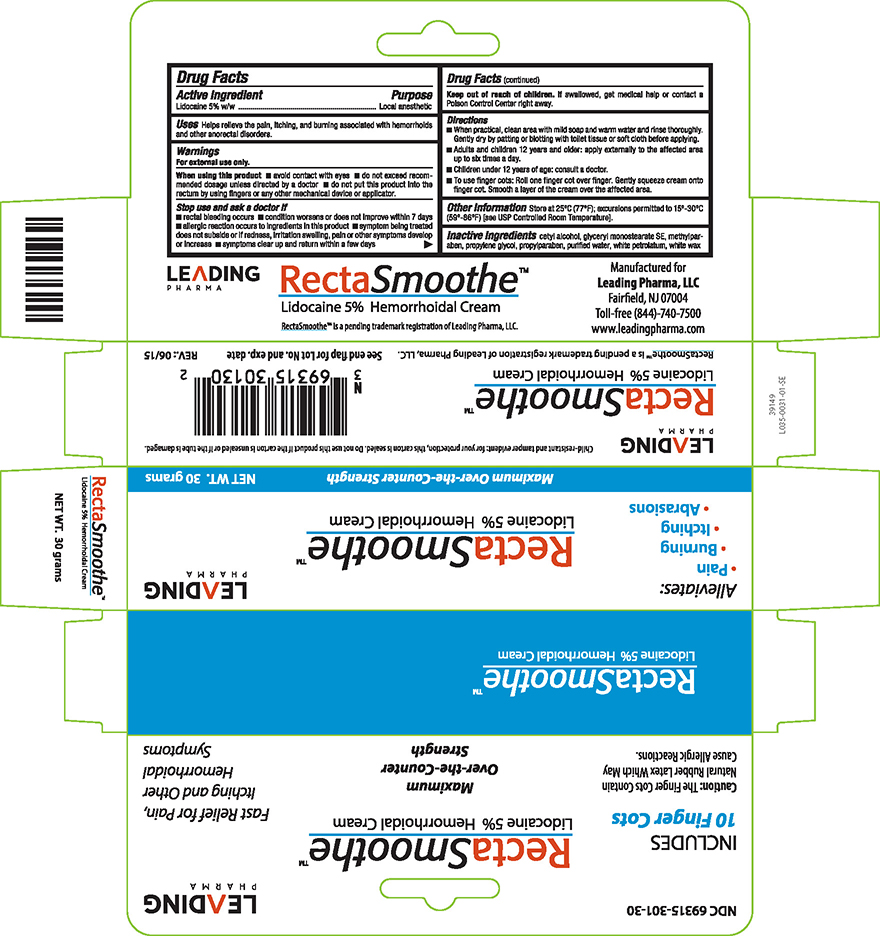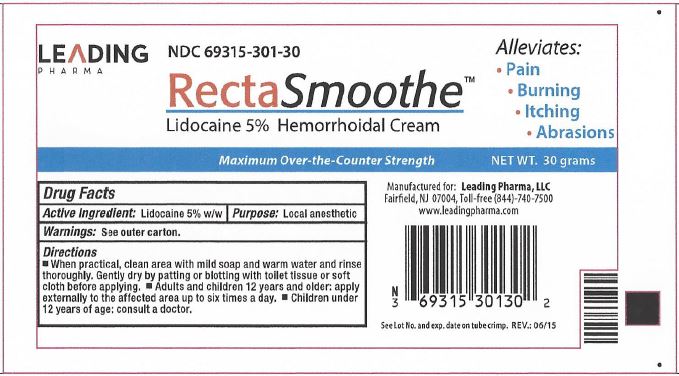 DRUG LABEL: RectaSmoothe
NDC: 69315-301 | Form: CREAM
Manufacturer: Leading Pharma, LLC
Category: otc | Type: HUMAN OTC DRUG LABEL
Date: 20171223

ACTIVE INGREDIENTS: LIDOCAINE 5 g/100 g
INACTIVE INGREDIENTS: WATER; CETYL ALCOHOL; GLYCERYL STEARATE SE; METHYLPARABEN; PROPYLENE GLYCOL; PROPYLPARABEN; PETROLATUM; WHITE WAX

Lidocaine 5%

Active Ingredient

Lidocaine 5% w/w

Purpose

Local anesthetic

Uses

Helps relive the pain, itching, and burning associated with hemorrhoids and other anorectal disorders.

WARNINGS:

For external use only.

When using this product

- avoid contact with the eyes
- do not exceed recommended dosage unless directed by a doctor
- do not put this product into the rectum by using fingers or any other mechanical device or applicator

Stop use and ask doctor if

- rectal bleeding occurs
- condition worsens or does not improve within 7 days
- allergic reaction occurs to ingredients in this product
- symptom being treated does not suside or if redness, irritation swelling, pain or other symptoms develop or increase
- symptoms clear up and return within a few days

Keep out of the reach of children

If swallowed, get medical help or contact a Poison Control Center right away.

Directions

- When practical, clean area with mild soap and warm water and rinse thouroughly. Gently dry by patting or blotting with toilet tissue or soft cloth before applying.
- Adults and children 12 years and older: Apply externally to the affected area up to six times a day.
- Children under 12 years of age: Consult a doctor
- To use finger cots: Roll one finger cot over finger. FGently squeeze cream onto finger cot. Smooth a layer of the cream over the affected area.

Other Information

Store at 25°C (77°F); excursions permitted to 15°-30°C (59°-86°F) [see USP Controlled Room Temperature].

Inactive Ingredients

cetyl alcohol, glyceryl monostearate SE, methylparaben, propylene glycol, propylparaben, purified water, white petrolatum, white wax